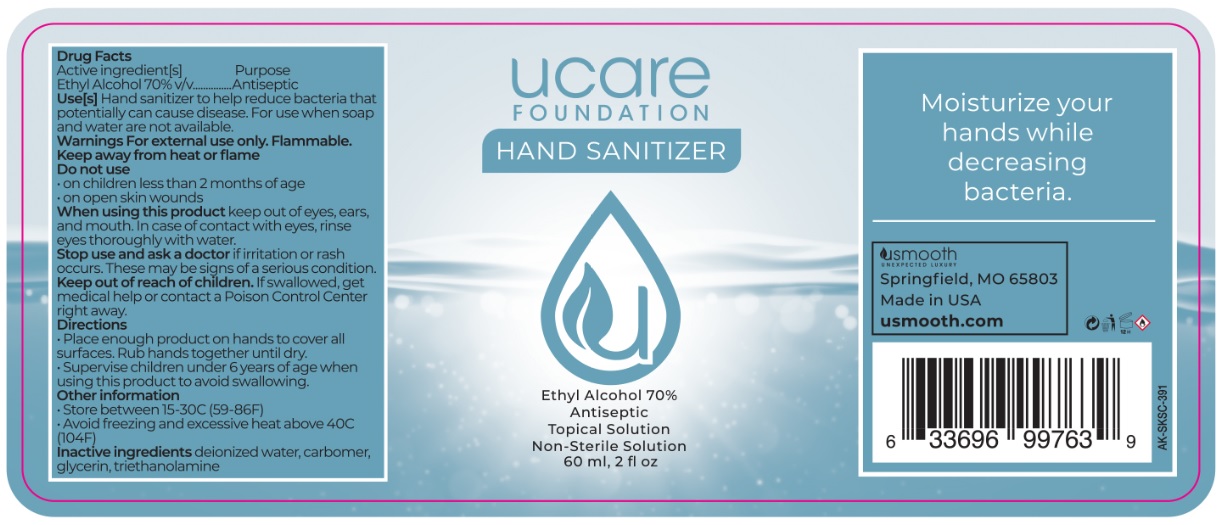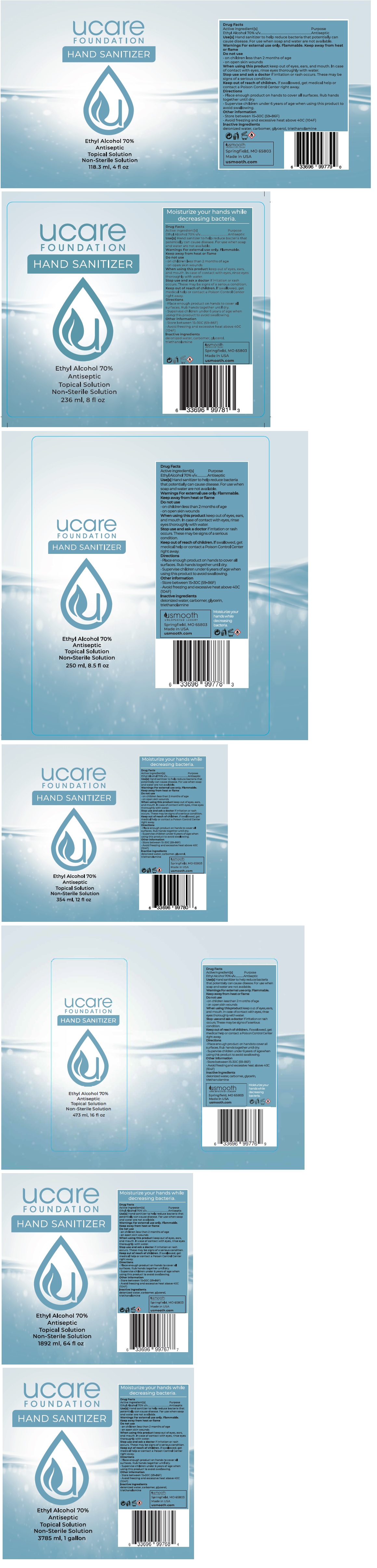 DRUG LABEL: UCARE HAND SANITIZER
NDC: 78086-905 | Form: SOLUTION
Manufacturer: Open Door Packaging, Llc
Category: otc | Type: HUMAN OTC DRUG LABEL
Date: 20200528

ACTIVE INGREDIENTS: ALCOHOL 70 mL/100 mL
INACTIVE INGREDIENTS: WATER; CARBOMER HOMOPOLYMER, UNSPECIFIED TYPE; GLYCERIN; TROLAMINE

ucare HAND SANITIZER

Active ingredient[s]

Ethyl Alcohol 70% v/v

Purpose

Antiseptic

INDICATIONS AND USAGE

Use[s] Hand Sanitizer to help reduce bacteria that potentially can cause disease. For use when soap and water are not available.

Warnings For external use only. Flammable.

Keep away from heat or flame

Do not use

• on children less than 2 months of age

• on open skin wounds

When using this product keep out of eyes, ears, and mouth. In case of contact with eyes, rinse eyes thoroughly with water.

Stop use and ask a doctor if irritation or rash occurs. These may be signs of a serious condition.

Keep out of reach of children. If swallowed, get medical help or contact a Poison Control Center right away.

Directions

• Place enough product on hands to cover all surfaces. Rub hands together until dry.

• Supervise children under 6 years of age when using this product to avoid swallowing.

Other Information

• Store between 15-30C (59-86F)
• Avoid freezing and excessive heat above 40C (104F)

INACTIVE INGREDIENT

Inactive ingredients deionized water, carbomer, glycerin, triethanolamine

ucare FOUNDATION

Non-Sterile Solution

Moisturize your hands while decreasing bacteria.

usmooth

UNEXPECTED LUXURY

Springfield, MO 65803

Made in USA

usmooth.com